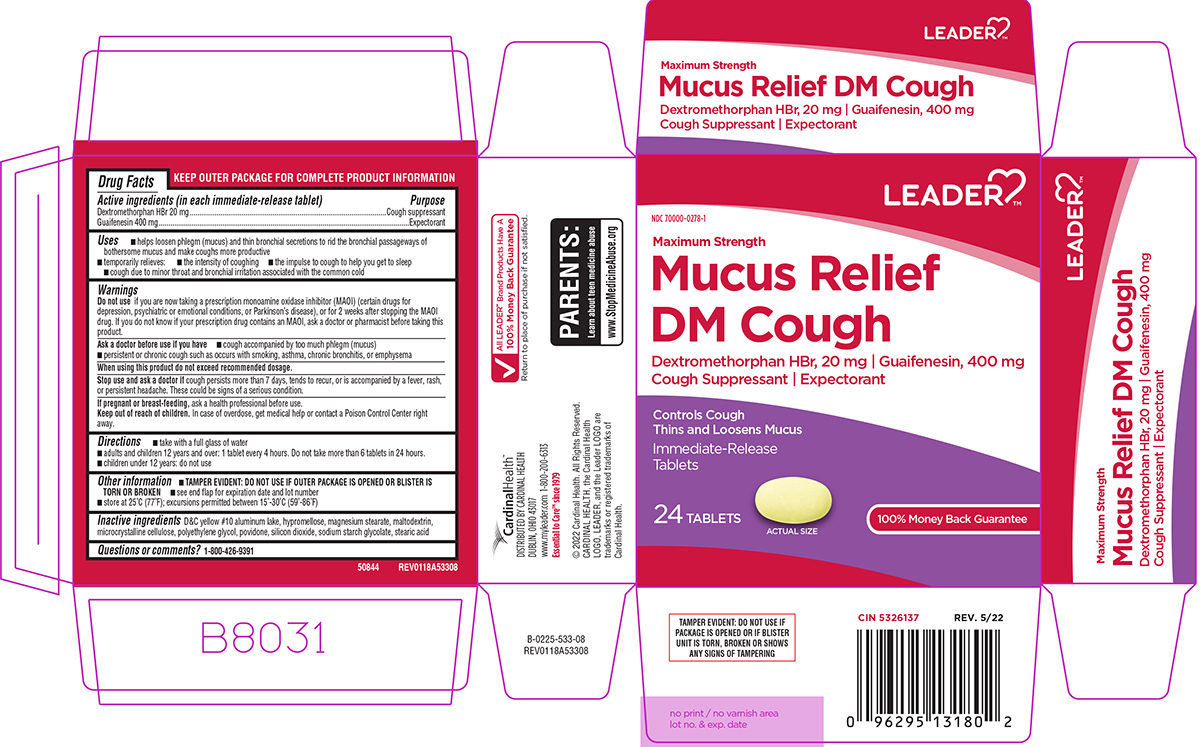 DRUG LABEL: Mucus Relief DM Cough
NDC: 70000-0278 | Form: TABLET, FILM COATED
Manufacturer: Cardinal Health 110, LLC. DBA Leader
Category: otc | Type: HUMAN OTC DRUG LABEL
Date: 20250508

ACTIVE INGREDIENTS: DEXTROMETHORPHAN HYDROBROMIDE 20 mg/1 1; GUAIFENESIN 400 mg/1 1
INACTIVE INGREDIENTS: D&C YELLOW NO. 10 ALUMINUM LAKE; HYPROMELLOSE, UNSPECIFIED; MAGNESIUM STEARATE; MALTODEXTRIN; MICROCRYSTALLINE CELLULOSE; POLYETHYLENE GLYCOL, UNSPECIFIED; POVIDONE, UNSPECIFIED; SILICON DIOXIDE; SODIUM STARCH GLYCOLATE TYPE A POTATO; STEARIC ACID

Leader 44-533

Active ingredients (in each immediate-release tablet)

Dextromethorphan HBr 20 mg
Guaifenesin 400 mg

Purpose

Cough suppressant
Expectorant

Uses

- helps loosen phlegm (mucus) and thin bronchial secretions to rid the bronchial passageways of bothersome mucus and make coughs more productive
- temporarily relieves:
  - cough due to minor throat and bronchial irritation associated with the common cold
  - the intensity of coughing
  - the impulse to cough to help you get to sleep

Warnings

Do not use

if you are now taking a prescription monoamine oxidase inhibitor (MAOI) (certain drugs for depression, psychiatric or emotional conditions, or Parkinson’s disease), or for 2 weeks after stopping the MAOI drug. If you do not know if your prescription drug contains an MAOI, ask a doctor or pharmacist before taking this product.

Ask a doctor before use if you have

- cough accompanied by too much phlegm (mucus)
- persistent or chronic cough such as occurs with smoking, asthma, chronic bronchitis, or emphysema

When using this product

do not exceed recommended dosage.

Stop use and ask a doctor if

cough persists more than 7 days, tends to recur, or is accompanied by a fever, rash, or persistent headache. These could be signs of a serious condition.

If pregnant or breast-feeding,

ask a health professional before use.

Keep out of reach of children.

In case of overdose, get medical help or contact a Poison Control Center right away.

Directions

- take with a full glass of water
- adults and children 12 years and over: 1 tablet every 4 hours. Do not take more than 6 tablets in 24 hours.
- children under 12 years: do not use

Other information

- TAMPER EVIDENT: DO NOT USE IF OUTER PACKAGE IS OPENED OR BLISTER IS TORN OR BROKEN
- see end flap for expiration date and lot number
- store at 25°C (77°F); excursions permitted between 15°-30°C (59°-86°F)

Inactive ingredients

D&C yellow #10 aluminum lake, hypromellose, magnesium stearate, maltodextrin, microcrystalline cellulose, polyethylene glycol, povidone, silicon dioxide, sodium starch glycolate, stearic acid

Questions or comments?

1-800-426-9391

Principal display panel

LEADER™

NDC 70000-0278-1

Maximum Strength
Mucus Relief
DM Cough

Dextromethorphan HBr, 20 mg ι Guaifenesin, 400 mg
Cough Suppressant ι Expectorant

Controls Cough
Thins and Loosens Mucus

Immediate-Release
Tablets

24 TABLETS

ACTUAL SIZE

100% Money Back Guarantee

TAMPER EVIDENT: DO NOT USE IF
PACKAGE IS OPENED OR IF BLISTER
UNIT IS TORN, BROKEN OR SHOWS
ANY SIGNS OF TAMPERING

50844 REV0118A53308

CardinalHealth™
DISTRIBUTED BY CARDINAL HEALTH
DUBLIN, OHIO 43017
www.myleader.com 1-800-200-6313
Essential to Care™ since 1979

© 2022 Cardinal Health. All Rights Reserved.
CARDINAL HEALTH, the Cardinal Health
LOGO, LEADER, and the Leader LOGO are
trademarks or registered trademarks of
Cardinal Health.

√ All LEADER™ Brand Products Have A
100% Money Back Guarantee
Return to place of purchase if not satisfied.

PARENTS:
Learn about teen medicine abuse
www.StopMedicineAbuse.org

Leader 44-533